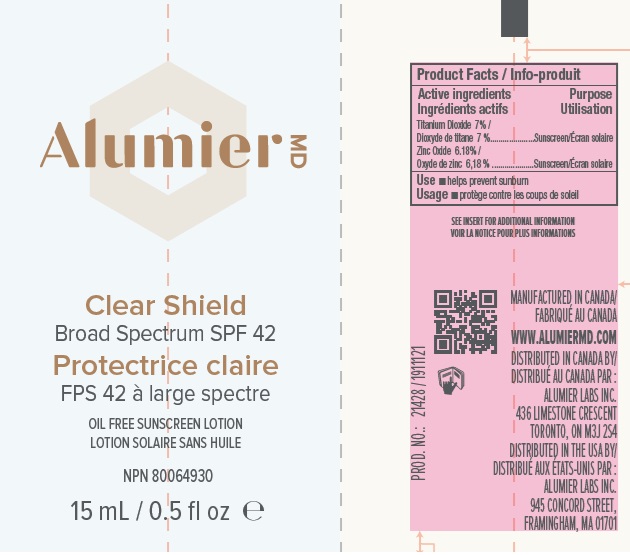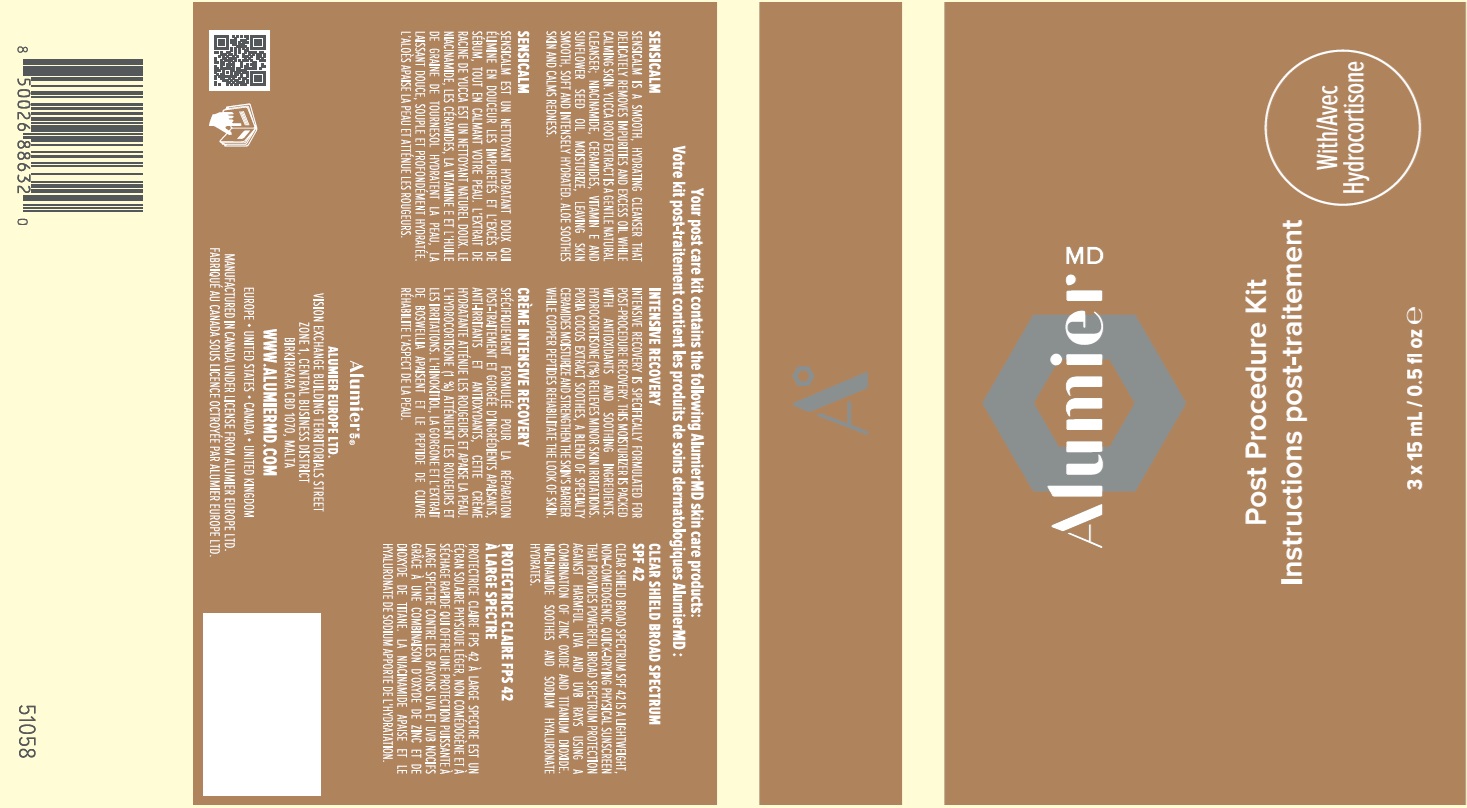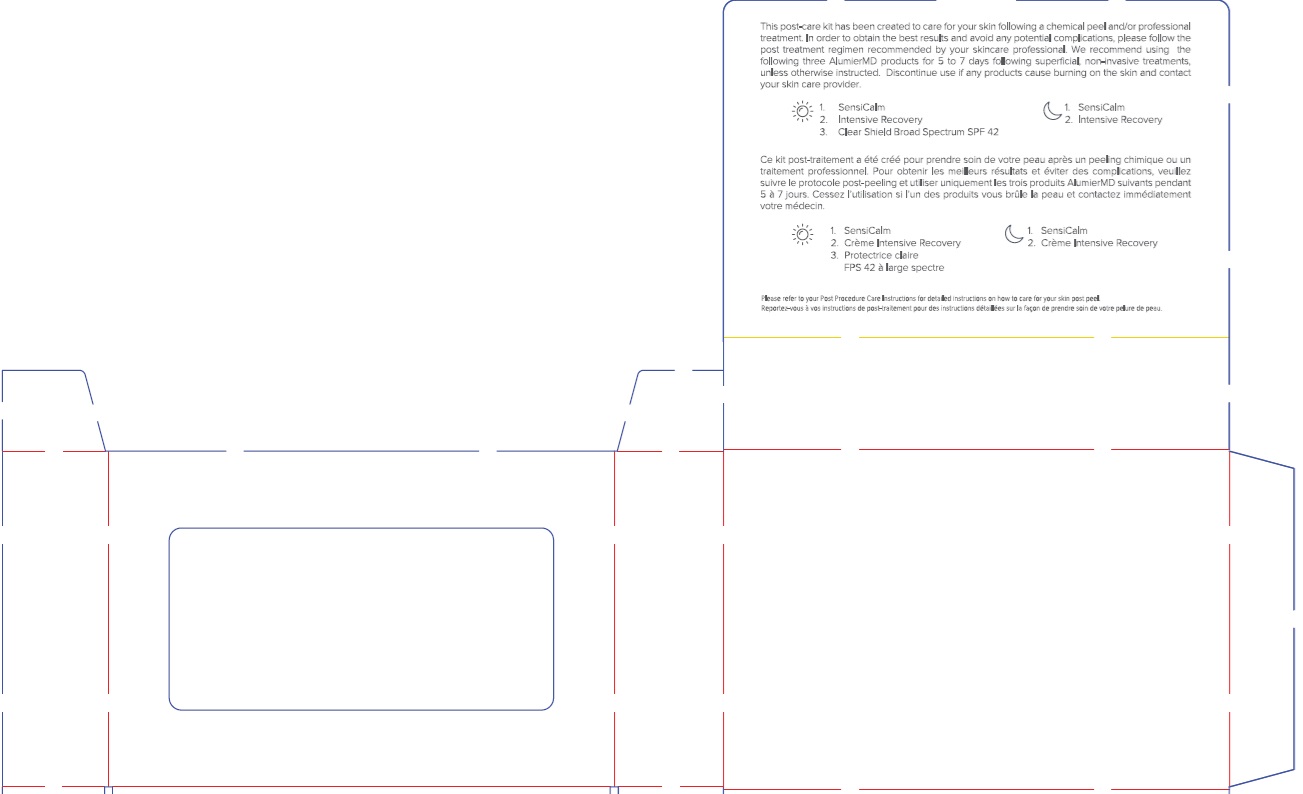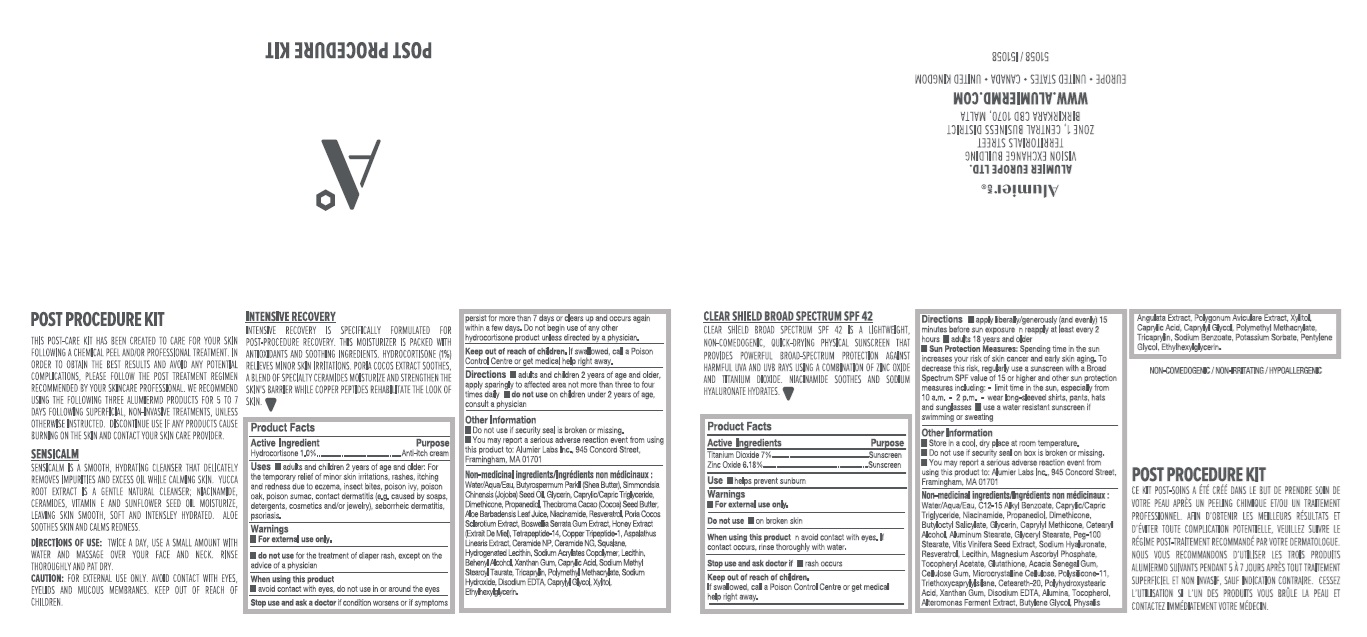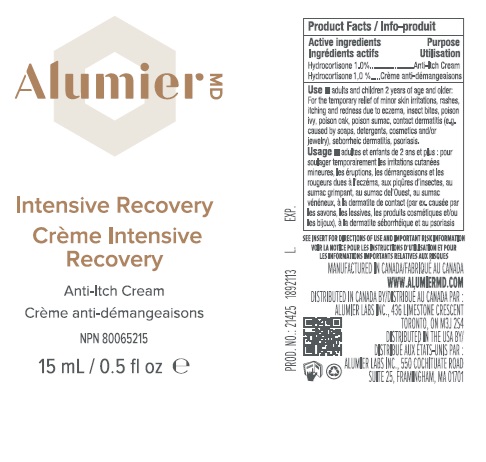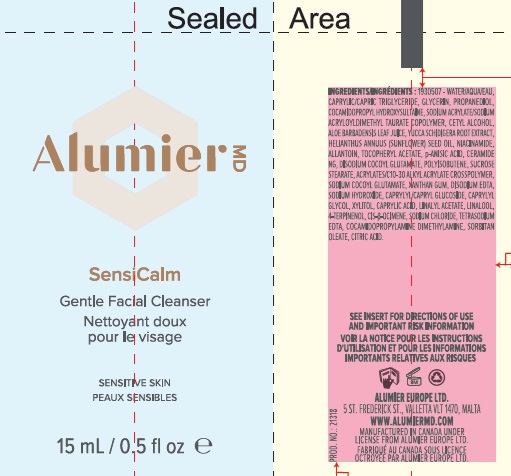 DRUG LABEL: Alumier MD Post Procedure Kit with Hydrocortisone
NDC: 69473-020 | Form: KIT | Route: TOPICAL
Manufacturer: Alumier Labs
Category: otc | Type: HUMAN OTC DRUG LABEL
Date: 20241025

ACTIVE INGREDIENTS: ZINC OXIDE 61.8 mg/1 mL; TITANIUM DIOXIDE 70 mg/1 mL; HYDROCORTISONE 10 mg/1 mL
INACTIVE INGREDIENTS: XYLITOL; CAPRYLIC ACID; ETHYLHEXYLGLYCERIN; HYALURONATE SODIUM; LECITHIN, SUNFLOWER; POLYHYDROXYSTEARIC ACID (2300 MW); BUTYLENE GLYCOL; TRICAPRYLIN; GLYCERYL MONOSTEARATE; NIACINAMIDE; CAPRYLYL METHICONE; POLYGONUM AVICULARE TOP; TRIETHOXYCAPRYLYLSILANE; WATER; ACACIA; POLYOXYL 20 CETOSTEARYL ETHER; MAGNESIUM ASCORBYL PHOSPHATE; BUTYLOCTYL SALICYLATE; GLYCERIN; VITIS VINIFERA SEED; ALUMINUM MONOSTEARATE; MEDIUM-CHAIN TRIGLYCERIDES; XANTHAN GUM; ALKYL (C12-15) BENZOATE; PROPANEDIOL; CARBOXYMETHYLCELLULOSE SODIUM, UNSPECIFIED FORM; .ALPHA.-TOCOPHEROL ACETATE; MICROCRYSTALLINE CELLULOSE; EDETATE DISODIUM; CETOSTEARYL ALCOHOL; PEG-100 STEARATE; ALUMINUM OXIDE; GLUTATHIONE; PHENOXYETHANOL; RESVERATROL; DIMETHICONE/VINYL DIMETHICONE CROSSPOLYMER (SOFT PARTICLE); TOCOPHEROL; PHYSALIS ANGULATA; POLY(METHYL METHACRYLATE; 450000 MW); SODIUM BENZOATE; DIMETHICONE; CAPRYLYL GLYCOL; PENTYLENE GLYCOL; POTASSIUM SORBATE; LECITHIN, SUNFLOWER; WATER; GLYCERIN; DIMETHICONE; DOCOSANOL; COCOA BUTTER; NIACINAMIDE; PREZATIDE COPPER; INDIAN FRANKINCENSE; HONEY; EDETATE DISODIUM; TRICAPRYLIN; XYLITOL; SODIUM METHYL STEAROYL TAURATE; XANTHAN GUM; ETHYLHEXYLGLYCERIN; MEDIUM-CHAIN TRIGLYCERIDES; PROPANEDIOL; SHEA BUTTER; JOJOBA OIL; RESVERATROL; ASPALATHUS LINEARIS LEAF; SQUALANE; ALOE VERA LEAF; POLY(METHYL METHACRYLATE; 450000 MW); SODIUM HYDROXIDE; CAPRYLYL GLYCOL; CAPRYLIC ACID; HYDROGENATED SOYBEAN LECITHIN; CERAMIDE NP; CERAMIDE NG

Alumier MD Post Procedure Kit with Hydrocortisone

Active Ingredients

Clear Shield:

Titanium Dioxide 7%

Zinc Oxide 6.18%

Intensive Recovery:

Hydrocortisone 1.0%

Purpose

Clear Shield:

Sunscreen

Intensive Recovery:

Anti-itch cream

Uses

Clear Shield:

- helps prevent sunburn

Intensive Recovery:

- adults and children 2 years of age and older: For the temporary relief of minor skin irritations, rashes, itching and redness due to eczema, insect bites, poison ivy, poison oak, poison sumac, contact dermatitis (e.g. caused by soaps, detergents, cosmetics and/or jewelry), seborrheic dermatitis, psoriasis.

Warnings

For external use only

Do not use

Clear Shield:

- on broken skin

Intensive Recovery:

- for the treatment of diaper rash, except on the advice of a physician

When using this product

Clear Shield:

- avoid contact with eyes. If contact occurs, rinse thoroughly with water.

Intensive Recovery:

- avoid contact with eyes, do not use in or around the eyes

Stop use and ask a doctor

Clear Shield:

- if rash occurs

Intensive Recovery:

- if condition worsens or if symptoms persist for more than 7 days or clears up and occurs again within a few days. Do not begin use of any other hydrocortisone product unless directed by a physician.

Keep out of reach of children

If swallowed, call a Poison Control Centre or get medical help right away.

Directions

Clear Shield:

- apply liberally/generously (and evenly) 15 minutes before sun exposure
- reapply at least every 2 hours
- Sun Protection Measures: Spending time in the sun increases your risk of skin cancer and early skin aging. To decrease this risk, regularly use a sunscreen with a Broad Spectrum SPF value of 15 or higher and other sun protection measures including: - limit time in the sun, especially from 10 a.m. - 2 p.m. - wear long-sleeved shirts, pants, hats and sunglasses
- use a water resistant sunscreen if swimming or sweating

Intensive Recovery:

- adults and children 2 years of age and older, apply sparingly to affected area not more than three to four times daily
- do not use on children under 2 years of age, consult a physician

Other Information

Clear Shield:

- Store in a cool, dry place at room temperature.
- Do not use if security seal on box is broken or missing.
- You may report a serious adverse reaction event from using this product to: Alumier Labs Inc., 945 Concord Street, Framingham, MA 01701

Intensive Recovery:

- Do not use if security seal on box is broken or missing.
- You may report a serious adverse reaction event from using this product to: Alumier Labs Inc., 945 Concord Street, Framingham, MA 01701

Non-medicinal ingredients

Clear Shield:

Water/Aqua/Eau, C12-15 Alkyl Benzoate, Caprylic/Capric Triglyceride, Niacinamide, Propanediol, Dimethicone, Butyloctyl Salicylate, Glycerin, Caprylyl Methicone, Cetearyl Alcohol, Aluminium Stearate, Glyceryl Stearate, PEG-100 Stearate, Vitis Vinifera Seed Extract, Sodium Hyaluronate, Resveratrol, Lecithin, Magnesium Ascorbyl Phosphate, Tocopheryl Acetate, Glutathione, Acacia Senegal Gum, Cellulose Gum, Microcrystalline Cellulose, Polysilicone-11, Triethoxycaprylylsilane, Ceteareth-20, Polyhydroxystearic Acid, Xanthan Gum, Disodium EDTA, Alumina, Tocopherol, Alteromonas Ferment Extract, Butylene Glycol, Physalis Angulata Extract, Polygonum Aviculare Extract, Xylitol, Caprylic Acid, Caprylyl Glycol, Polymethyl Methacrylate, Tricaprylin, Sodium Benzoate, Potassium Sorbate, Pentylene Glycol, Ethylhexylglycerin.

Intensive Recovery:

Water/Aqua/Eau, Butyrospermum Parkii (Shea Butter), Simmondsia Chinensis (Jojoba) Seed Oil, Glycerin, Caprylic/Capric Triglyceride, Dimethicone, Propanediol, Theobroama Cacao (Cocoa) Seed Butter, Aloe Barbadensis Leaf Juice, Niacinamide, Resveratrol, Poria Cocos Sclerotium Extract, Boswellia Serrata Gum Extract, Honey Extract (Extait De. Miel), Tetrapeptide-14, Copper Tripeptide-1, Aspalathus Linearis Extract, Ceramide NP, Ceramide NG, Squalane, Hydrogenated Lecithin, Sodium Acrylates Copolymer, Lecithin, Behenyl Alchol, Xanthan Gum, Caprylic Acid, Sodium Methyl Stearoyl Taurate, Tricaprylin, Polymethyl Methacrylate, Sodium Hydroxide, Disodium EDTA, Caprylyl Glycol, Xylitol, Ethylhexylglycerin.